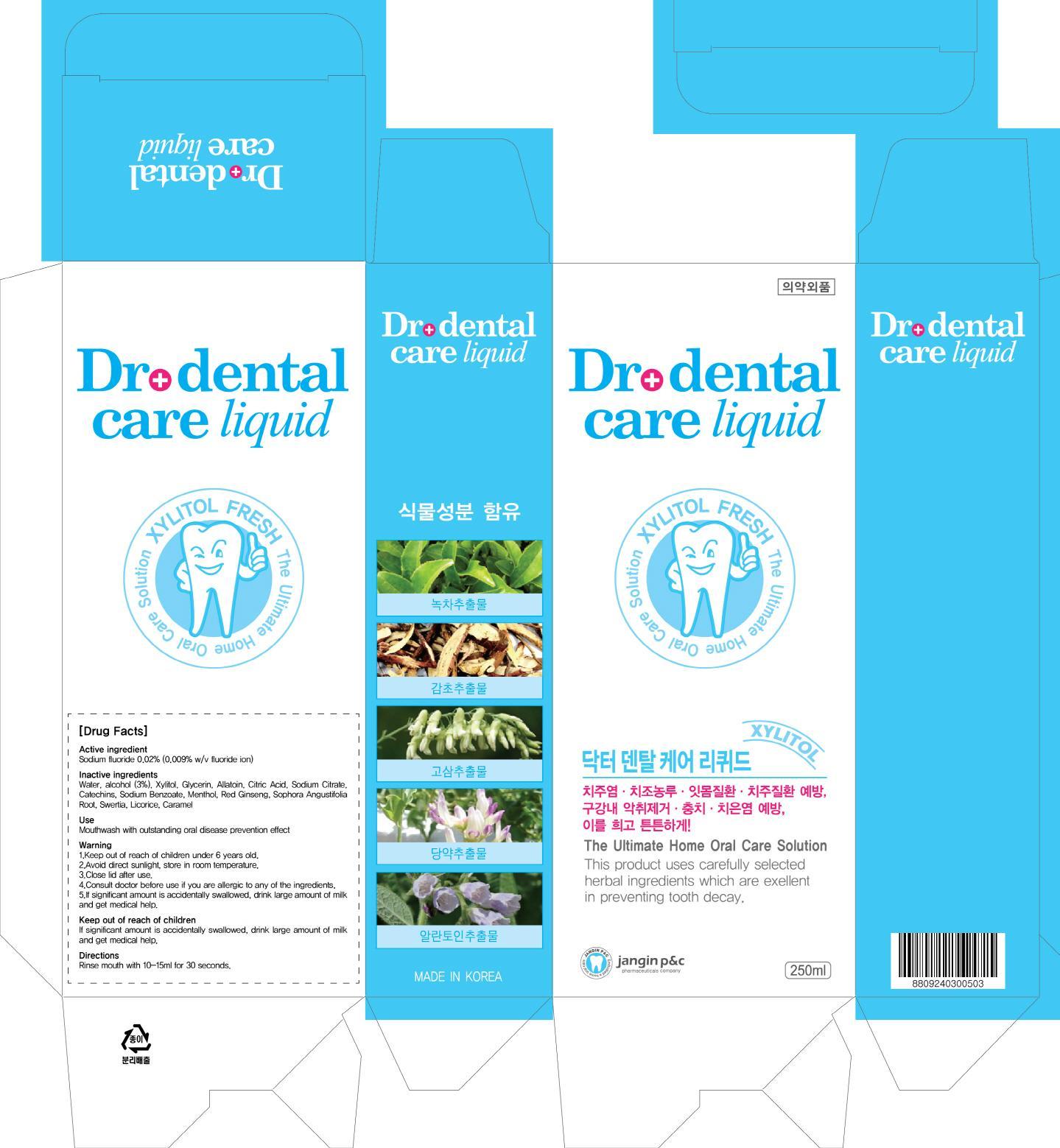 DRUG LABEL: DR DENTAL CARE 250ML
NDC: 69255-020 | Form: LIQUID
Manufacturer: Jangin Pharm Co., Ltd.
Category: otc | Type: HUMAN OTC DRUG LABEL
Date: 20140929

ACTIVE INGREDIENTS: SODIUM FLUORIDE 0.05 mg/250 mL
INACTIVE INGREDIENTS: Water; Alcohol

ACTIVE INGREDIENT

Sodium fluoride 0.02% (0.009% w/v fluoride ion)

INACTIVE INGREDIENT

Inactive ingredients:
Water, Alcohol (3%), Xylitol, Glycerin, Allantoin, Citric Acid, Sodium Citrate, Catechins, Sodium Benzoate, Menthol, Red Ginseng, Sophora Angustifolia Root, Swertia, Licorice, Caramel

PURPOSE

Purpose: Anticavity

WARNINGS

Warning:
1. Keep out of reach of children under 6 years old.
2. Avoid direct sunlight, store in room temperature.
3. Close lid after use.
4. Consult doctor before use if you are allergic to any of the ingredients.
5. If significant amount is accidentally swallowed, drink large amount of milk and get medical help.

KEEP OUT OF REACH OF CHILDREN

If significant amount is accidentally swallowed, drink large amount of milk and get medical help.

Use

Mouthwash with outstanding oral disease prevention effect

Directions

Rinse mouth with 10-15ml for 30 seconds.